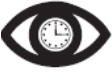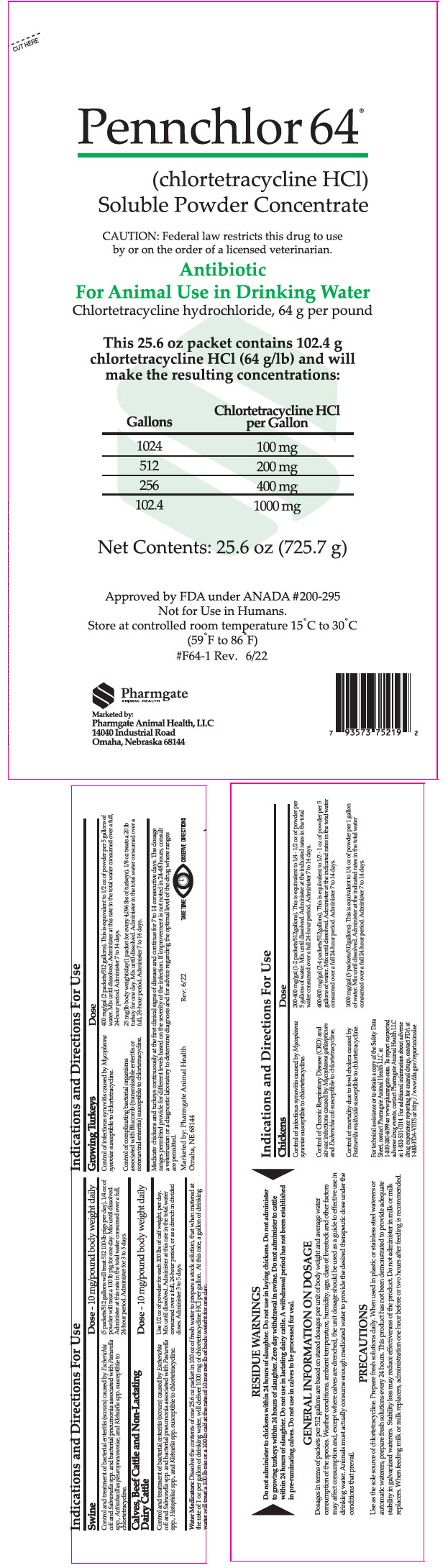 DRUG LABEL: Pennchlor 64
NDC: 51429-064 | Form: POWDER
Manufacturer: Pharmgate Animal Health
Category: animal | Type: PRESCRIPTION ANIMAL DRUG LABEL
Date: 20221026

ACTIVE INGREDIENTS: Chlortetracycline Hydrochloride 0.141 g/1 g

Pennchlor 64®
(Chlortetracycline HCl)
Soluble Powder Concentrate

RESIDUE WARNINGS

Do not administer to chickens within 24 hours of slaughter. Do not use in laying chickens. Do not administer to growing turkeys within 24 hours of slaughter. Zero day withdrawal in swine. Do not administer to cattle within 24 hours of slaughter. Do not use in lactating dairy cattle. A withdrawal period has not been established in pre-ruminating calves. Do not use in calves to be processed for veal.

GENERAL INFORMATION ON DOSAGE

Dosages in terms of packets per 512 gallons are based on stated dosages per unit of body weight and average water consumption of the species. Weather conditions, ambient temperature, humidity, age, class of livestock and other factors may affect consumption and, except where calves are drenched, the unit dosage should be used as a guide to effective use in drinking water. Animals must actually consume enough medicated water to provide the desired therapeutic dose under the conditions that prevail.

PRECAUTIONS

Use as the sole source of chlortetracycline. Prepare fresh solutions daily. When used in plastic or stainless steel waterers or automatic waterers, prepare fresh solutions every 24 hours. This product has not been demonstrated to provide adequate stability in galvanized waterers. Stability loss may reduce effectiveness of the product. Do not administer in milk or milk replacers. When feeding milk or milk replacers, administration one hour before or two hours after feeding is recommended.

Indications and Directions For Use

Chickens | Dose
Control of infectious synovitis caused by Mycoplasma synoviae susceptible to chlortetracycline. | 200-400 mg/gal (1-2 packets/512 gallons). This is equivalent to ¼ - ½ oz of powder per 5 gallons of water. Mix until dissolved. Administer at the indicated rates in the total water consumed over a full 24-hour period. Administer 7 to 14 days.
Control of Chronic Respiratory Disease (CRD) and air-sac infections caused by Mycoplasma gallisepticum and Escherichia coli susceptible to chlortetracycline. | 400-800 mg/gal (2-4 packets/512 gallons). This is equivalent to ½ - 1 oz of powder per 5 gallons of water. Mix until dissolved. Administer at the indicated rates in the total water consumed over a full 24-hour period. Administer 7 to 14 days.
Control of mortality due to fowl cholera caused by Pasteurella multocida susceptible to chlortetracycline. | 1000 mg/gal (5 packets/512 gallons). This is equivalent to ¼ oz of powder per 1 gallon of water. Mix until dissolved. Administer at the indicated rates in the total water consumed over a full 24-hour period. Administer 7 to 14 days.

Growing Turkeys | Dose
Control of infectious synovitis caused by Mycoplasma synoviae susceptible to chlortetracycline. | 400 mg/gal (2 packets/512 gallons). This is equivalent to ½ oz of powder per 5 gallons of water. Mix until dissolved. Administer at this rate in the total water consumed over a full 24-hour period. Administer 7 to 14 days.
Control of complicating bacterial organisms associated with Bluecomb (transmissible enteritis or coronaviral enteritis) susceptible to chlortetracycline. | 25 mg/lb body weight/day (1 packet for every 4,096 lbs of turkeys). ⅛ oz treats a 20 lb turkey for one day. Mix until dissolved. Administer in the total water consumed over a full 24 hour period. Administer 7 to 14 days.

Medicate chickens and turkeys continuously at the first clinical signs of disease and continue for 7 to 14 consecutive days. The dosage ranges permitted provide for different levels based on the severity of the infection. If improvement is not noted in 24-48 hours, consult a veterinarian or a diagnostic laboratory to determine diagnoses and for advice regarding the optimal level of the drug where ranges are permitted.

Swine | Dose – 10 mg/pound body weight daily
Control and treatment of bacterial enteritis (scours) caused by Escherichia coli and Salmonella spp. and bacterial pneumonia associated with Pasturella spp., Actinobacillus pleuropneumoniae, and Klebsiella spp. susceptible to chlortetracycline. | (5 packets/512 gallons will treat 512 100-lb pigs per day). ¼ oz of powder will treat a 100 lb pig for one day. Mix until dissolved. Administer at this rate in the total water consumed over a full 24-hour period. Administer for 3 to 5 days.

Calves, Beef Cattle and Non-Lactating Dairy Cattle | Dose – 10 mg/pound body weight daily
Control and treatment of bacterial enteritis (scours) caused by Escherichia coli and Salmonella spp. and bacterial pneumonia associated with Pasturella spp., Histophilus spp., and Klebsiella spp. susceptible to chlortetracycline. | Use ½ oz. of powder for each 200 lbs of calf weight, per day. Mix until dissolved. Administer at this rate in the total water consumed over a full, 24-hour period, or as a drench in divided doses. Administer 3 to 5 days.

Water Medicators: Dissolve the contents of one 25.6 oz packet in 100 oz of fresh water to prepare a stock solution, that when metered at the rate of 1 oz per gallon of drinking water, will deliver 1000 mg of chlortetracycline HCl per gallon. At this rate, a gallon of drinking water will treat a 100 lb pig or a 100 lb calf at the rate of 10 mg per lb of body weight for one day.

For technical assistance or to obtain a copy of the Safety Data Sheet, contact Pharmgate Animal Health LLC at 1-800-380-6099 or www.pharmgate.com. To report suspected adverse drug events, contact Pharmgate Animal Health LLC at 1-833-531-0114. For additional information about adverse drug experience reporting for animal drugs, contact FDA at 1-888-FDA-VETS or http://www.fda.gov/reportanimalae

Take TimeObserve Directions

PRINCIPAL DISPLAY PANEL - 725.7 g Packet Label

CUT HERE

Pennchlor 64®
(chlortetracycline HCl)
Soluble Powder Concentrate

CAUTION: Federal law restricts this drug to use
by or on the order of a licensed veterinarian.

Antibiotic
For Animal Use in Drinking Water
Chlortetracycline hydrochloride, 64 g per pound

This 25.6 oz packet contains 102.4 g
chlortetracycline HCl (64 g/lb) and will
make the resulting concentrations:

Gallons | Chlortetracycline HCl per Gallon
1024 | 100 mg
512 | 200 mg
256 | 400 mg
102.4 | 1000 mg

Net Contents: 25.6 oz (725.7 g)

Approved by FDA under ANADA #200-295
Not for Use in Humans.
Store at controlled room temperature 15°C to 30°C
(59°F to 86°F)
#F64-1 Rev. 6/22

Pharmgate
ANIMAL HEALTH

Marketed by:
Pharmgate Animal Health, LLC
14040 Industrial Road
Omaha, Nebraska 68144